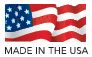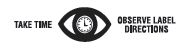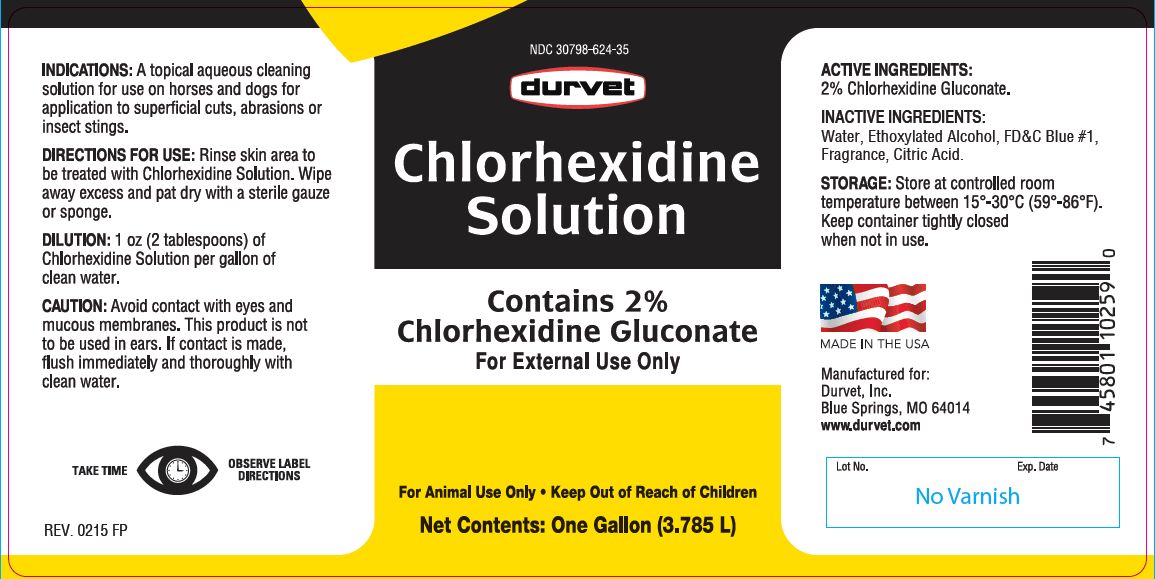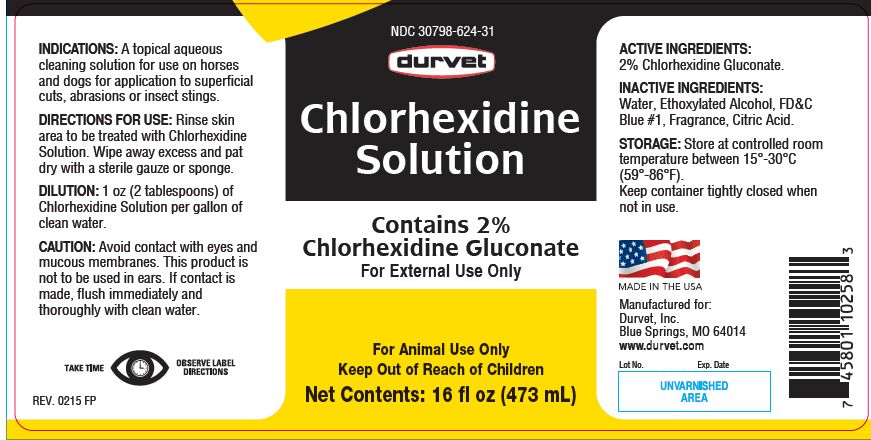 DRUG LABEL: CHLORHEXIDINE
NDC: 30798-624 | Form: SOLUTION
Manufacturer: Durvet
Category: animal | Type: OTC ANIMAL DRUG LABEL
Date: 20191014

ACTIVE INGREDIENTS: CHLORHEXIDINE GLUCONATE 99.0 g/1 L

Chlorhexidine Solution
Contains 2% Chlorhexidine Gluconate

KEEP OUT OF REACH OF CHILDREN

For External Use Only

For Animal Use Only
Keep Out of Reach of Children

INDICATIONS:

A topical aqueous cleaning solution for use on horses and dogs for application to superficial cuts, abrasions or insect stings.

DIRECTIONS FOR USE:

Rinse skin area to be treated with Chlorhexidine Solution. Wipe away excess and pat dry with a sterile gauze or sponge.

DILUTION:

1 oz (2 tablespoons) of Chlorhexidine Solution per gallon of clean water.

CAUTION:

Avoid contact with eyes and mucous membranes. This product is not to be used in ears. If contact is made, flush immediately and thoroughly with clean water.

ACTIVE INGREDIENTS:

2% Chlorhexidine Gluconate.

INACTIVE INGREDIENTS:

Water, Ethoxylated Alcohol, FD&C Blue #1, Fragrance, Citric Acid.

STORAGE:

Store at controlled room temperature between 15°-30°C (59°-86°F).
Keep container tightly closed when not in use.

Net Contents:

16 fl oz (473 mL) REV. 0215 FP

One Gallon (3.785 L) REV. 0215 FP

INFORMATION FOR OWNERS/CAREGIVERS

Manufactured for:
Durvet, Inc.
Blue Springs, MO 64014
www.durvet.com